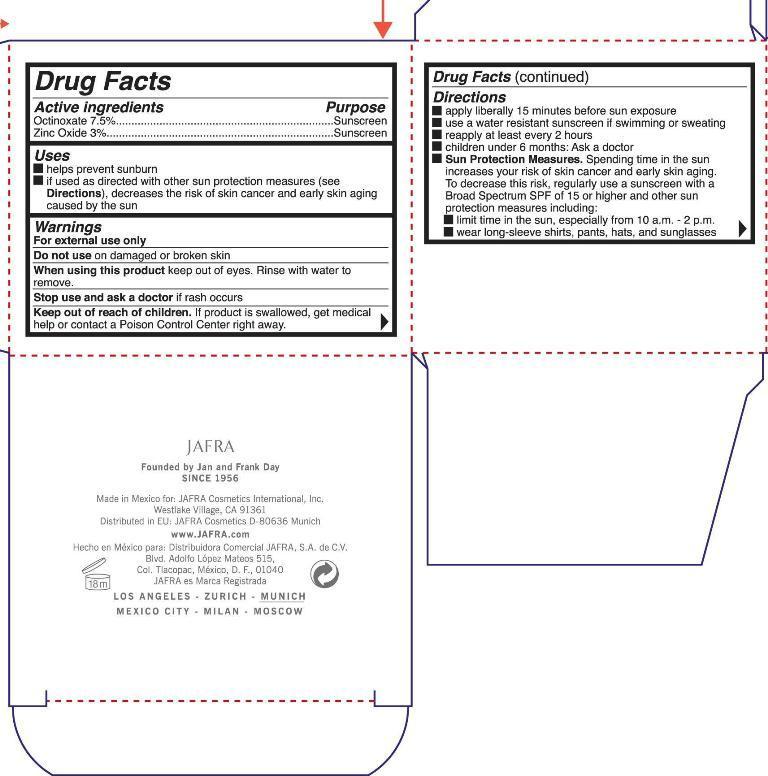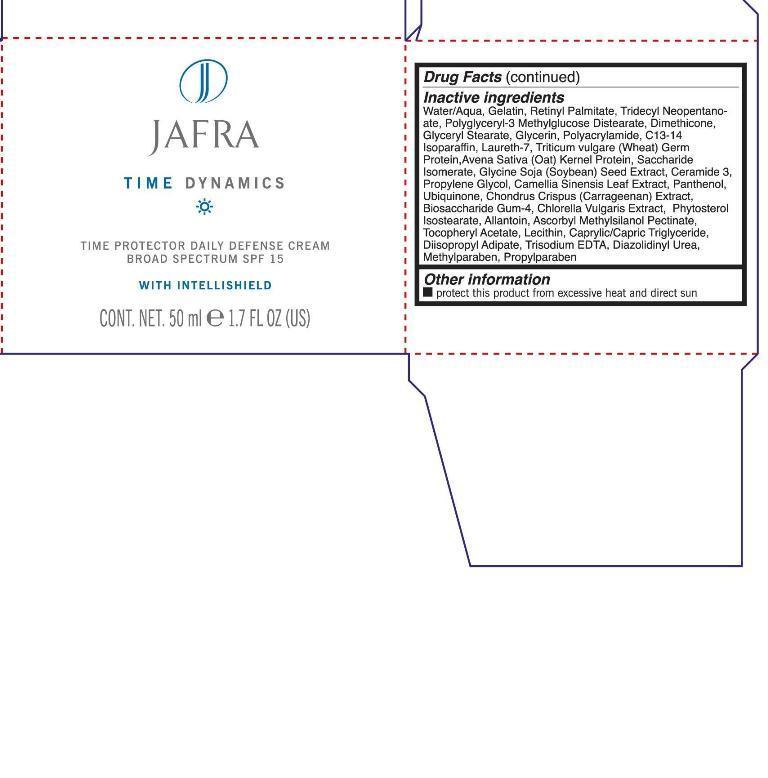 DRUG LABEL: Daily Defense SPF 15
NDC: 68828-131 | Form: CREAM
Manufacturer: Jafra Cosmetics International Inc
Category: otc | Type: HUMAN OTC DRUG LABEL
Date: 20181206

ACTIVE INGREDIENTS: OCTINOXATE 7.5 g/100 mL; ZINC OXIDE 3 g/100 mL
INACTIVE INGREDIENTS: WATER; VITAMIN A PALMITATE; TRIDECYL NEOPENTANOATE; DIMETHICONE; GLYCERYL MONOSTEARATE; GLYCERIN; POLYACRYLAMIDE (1500 MW); C13-14 ISOPARAFFIN; LAURETH-7; WHEAT GERM; SACCHARIDE ISOMERATE; CERAMIDE 3; PROPYLENE GLYCOL; GREEN TEA LEAF; PANTHENOL; CHONDRUS CRISPUS; CHLORELLA VULGARIS; ALLANTOIN; ASCORBYL METHYLSILANOL PECTINATE; .ALPHA.-TOCOPHEROL ACETATE; LECITHIN, SOYBEAN; MEDIUM-CHAIN TRIGLYCERIDES; DIISOPROPYL ADIPATE; EDETATE TRISODIUM; DIAZOLIDINYL UREA; METHYLPARABEN; PROPYLPARABEN

Time Protector Daily Defense Cream Broad Spectrum SPF 15

Active ingredients purpose

Octinoxate 7.5% Sunscreen

Zinc Oxide 3% Sunscreen

Uses

Helps prevent sunburn

If used as directed with other sun protection measures (see directions), decreases the risk of skin cancer and early skin aging caused by the sun.

Keep out of reach of children. If product is swallowed, get medical help or contact a Poison Control Center right away.

Stop use and ask a doctor if rash occurs

Warnings

For external use only

Do not use on damaged or broken skin

When using this product keep out of eyes. Rinse with water to remove.

Directions

apply lliberally 15 minutes before sun exposure

use a water resistant sunscreen if swimming or sweating

reapply at least every 2 hours

children under 6 months: Ask a doctor

Sun Protection Measures. Spending time in the sun increases your risk of skin cancer and early skin aging.To decrease this risk regularly use a sunscreen with a Broad Spectrum SPF value of 15 or higher and other sun protection measures including:

limit time in the sun, especially from 10 a.m. - 2p.m.

wear long sleeve shirts, pants, hats, and sunglasses.

INACTIVE INGREDIENT

Water/Aqua, Gelatin, Retinyl Palmitate, Tridecyl Neopentanoate, Polyglyceryl-3 Methylglucose Distearate, Dimethicone, Glyceryl Stearate, Glycerin, Polyacrylamide, C13-14 Isoparaffin, Laureth-7, Triticum vulgare (Wheat) Germ Protein, Avena Sativa (Oat) Kernel Protein, Saccharide Isomerate, Glycine Soja (Soybean) Seed Extract, Ceramide 3, Propylene Glycol, Camellia Sinensis Leaf Extract, Panthenol, Ubiquinone, Chondrus Crispus (Carrageenan) Extract, Biosaccharide Gum-4, Chlorella Vulgaris extract, Phytosterol Isostearate, Allantoin, Ascorbyl Methylsilanol Pectinate, Tocopheryl Acetate, Lecithin, Caprylic/Capric Triglyceride, Diisopropyl Adipate, Trisodium EDTA, Diazolidnyl Urea, Methylparaben, Propylparaben.

PACKAGE LABEL

Jafra Time Dynamics

Time Dynamics

Time Protector Daily Defense Cream

Broad Spectrum SPF 15 with intellishield

cont. Net. 50 ml 1.7 Fl Oz (US)